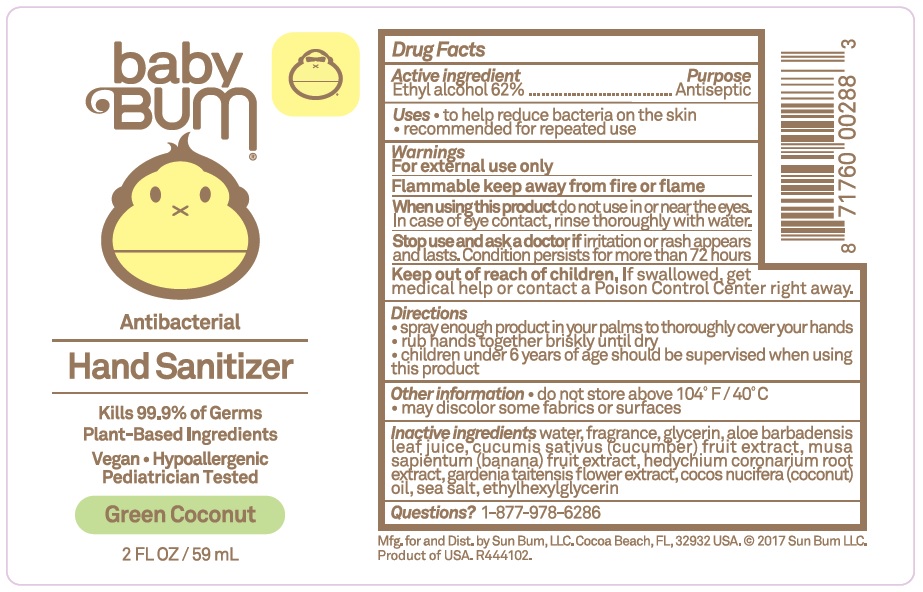 DRUG LABEL: Baby Bum Hand Sanitizer
NDC: 69039-614 | Form: LIQUID
Manufacturer: Sun Bum LLC
Category: otc | Type: HUMAN OTC DRUG LABEL
Date: 20220204

ACTIVE INGREDIENTS: ALCOHOL 0.62 mL/1 mL
INACTIVE INGREDIENTS: WATER; GLYCERIN; ALOE VERA LEAF; CUCUMBER; BANANA; HEDYCHIUM CORONARIUM ROOT; GARDENIA TAITENSIS FLOWER; COCONUT OIL; SEA SALT; ETHYLHEXYLGLYCERIN

Baby Bum Hand Sanitizer

Active ingredient

Ethyl alcohol 62%

Purpose

Antiseptic

Uses

- to help reduce bacteria on the skin
- recommended for repeated use

Warnings

For external use only

Flammable keep away from fire or flame

When using this product

do not use in or near the eyes. In case of eye contact, rinse thoroughly with water.

Stop use and ask a doctor if

irritation or rash appears and lasts. Condition persists for more than 72 hours

Keep out of reach of children.

If swallowed, get medical help or contact a Poison Control Center right away.

Directions

- spray enough product in your palms to thoroughly cover your hands
- rub hands together briskly until dry
- children under 6 years of age should be supervised when using this product

Other information

- do not store above 104° F/40°C
- may discolor some fabrics or surfaces

Inactive ingredients

water,fragrance,glycerin,aloe barbadensis leaf juice, cucumis sativus (cucumber) fruit extract, musa sapientum (banana) fruit extract, hedychium coronarium root extract, gardenia taitensis flower extract, cocos nucifera (coconut) oil, sea salt, ethylhexylglycerin

Questions?

1-877-978-6286